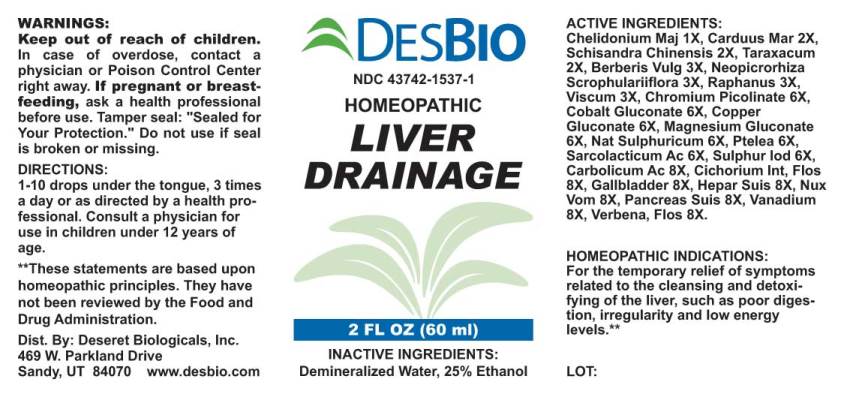 DRUG LABEL: Liver Drainage
NDC: 43742-1537 | Form: LIQUID
Manufacturer: Deseret Biologicals, Inc.
Category: homeopathic | Type: HUMAN OTC DRUG LABEL
Date: 20210615

ACTIVE INGREDIENTS: CHELIDONIUM MAJUS 1 [hp_X]/1 mL; MILK THISTLE 2 [hp_X]/1 mL; SCHISANDRA CHINENSIS FRUIT 2 [hp_X]/1 mL; TARAXACUM OFFICINALE 2 [hp_X]/1 mL; BERBERIS VULGARIS ROOT BARK 3 [hp_X]/1 mL; NEOPICRORHIZA SCROPHULARIIFLORA ROOT 3 [hp_X]/1 mL; RADISH 3 [hp_X]/1 mL; VISCUM ALBUM FRUITING TOP 3 [hp_X]/1 mL; CHROMIUM PICOLINATE 6 [hp_X]/1 mL; COBALTOUS GLUCONATE 6 [hp_X]/1 mL; COPPER GLUCONATE 6 [hp_X]/1 mL; MAGNESIUM GLUCONATE 6 [hp_X]/1 mL; SODIUM SULFATE 6 [hp_X]/1 mL; PTELEA TRIFOLIATA BARK 6 [hp_X]/1 mL; LACTIC ACID, L- 6 [hp_X]/1 mL; SULFUR IODIDE 6 [hp_X]/1 mL; PHENOL 8 [hp_X]/1 mL; CICHORIUM INTYBUS FLOWER 8 [hp_X]/1 mL; SUS SCROFA GALLBLADDER 8 [hp_X]/1 mL; PORK LIVER 8 [hp_X]/1 mL; STRYCHNOS NUX-VOMICA SEED 8 [hp_X]/1 mL; SUS SCROFA PANCREAS 8 [hp_X]/1 mL; VANADIUM 8 [hp_X]/1 mL; VERBENA OFFICINALIS FLOWERING TOP 8 [hp_X]/1 mL
INACTIVE INGREDIENTS: WATER; ALCOHOL

Drug Facts:

ACTIVE INGREDIENTS:

Chelidonium Majus 1X, Carduus Marianus 2X, Schisandra Chinensis 2X, Taraxacum Officinale 2X, Berberis Vulgaris 3X, Neopicrorhiza Scrophulariiflora 3X, Raphanus Sativus 3X, Viscum Album 3X, Chromium Picolinate 6X, Cobalt Gluconate 6X, Copper Gluconate 6X, Magnesium Gluconate 6X, Natrum Sulphuricum 6X, Ptelea Trifoliata 6X, Sarcolacticum Acidum 6X, Sulphur Iodatum 6X, Carbolicum Acidum 8X, Cichorium Intybus, Flos 8X, Gallbladder (Suis) 8X, Hepar Suis 8X, Nux Vomica 8X, Pancreas Suis 8X, Vanadium Metallicum 8X, Verbena Officinalis, Flos 8X.

HOMEOPATHIC INDICATIONS:

For the temporary relief of symptoms related to the cleansing and detoxifying of the liver, such as poor digestion, irregularity and low energy levels.**

**These statements are based upon traditional homeopathic practice. They have not been reviewed by the Food and Drug Administration.

WARNINGS:

Keep out of reach of children. In case of overdose, contact a physician or Poison Control Center right away.

If pregnant or breast-feeding, seek advice of a health professional before use.

Tamper seal: "Sealed for Your Protection." Do not use if seal is broken or missing.

Keep out of reach of children. In case of overdose, contact a physician or Poison Control Center right away.

DIRECTIONS:

1-10 drops under the tongue, 3 times a day or as directed by a health professional. Consult a physician for use in children under 12 years of age.

HOMEOPATHIC INDICATIONS:

For the temporary relief of symptoms related to the cleansing and detoxifying of the liver, such as poor digestion, irregularity and low energy levels.**

**These statements are based upon traditional homeopathic practice. They have not been reviewed by the Food and Drug Administration.

INACTIVE INGREDIENTS:

Demineralized Water, 25% Ethanol.

QUESTIONS:

Dist. By: Deseret Biologicals, Inc.

469 W. Parkland Drive

Sandy, UT 84070 www.desbio.com

PACKAGE LABEL DISPLAY:

DESBIO

NDC 43742-1537-1

HOMEOPATHIC

LIVER DRAINAGE

2 FL OZ (60 ml)